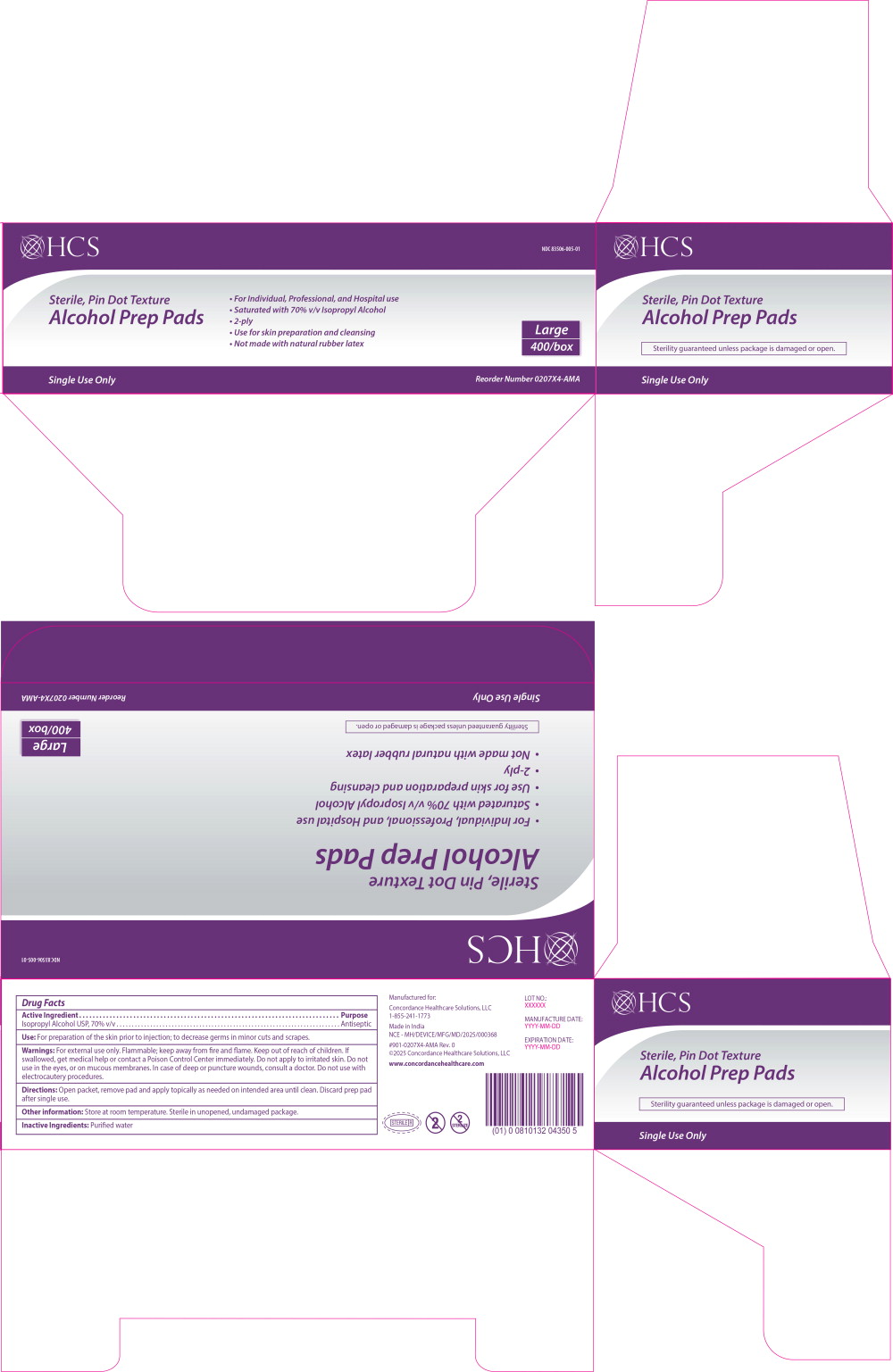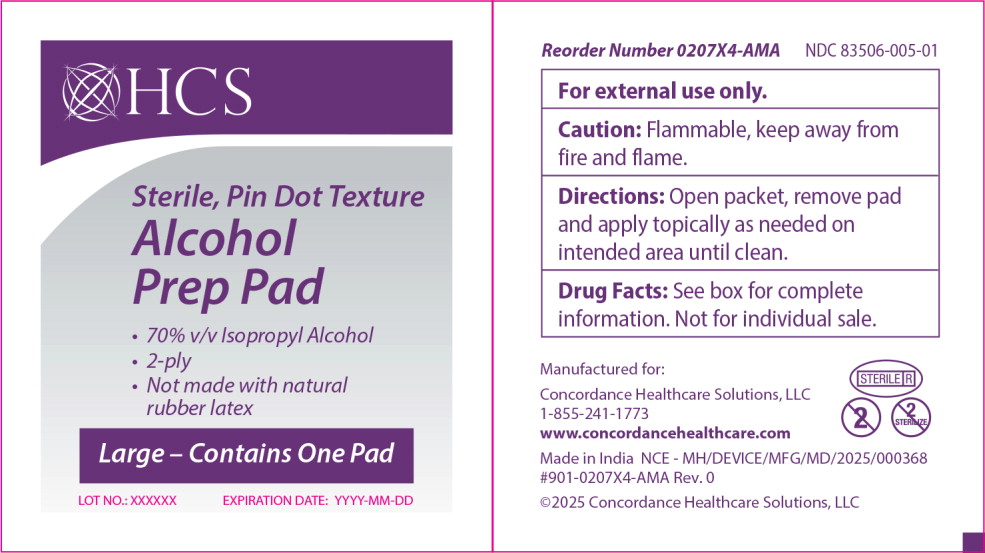 DRUG LABEL: HCS Alcohol Prep Pad Large
NDC: 83506-005 | Form: SWAB
Manufacturer: Concordance Healthcare Solutions, LLC.
Category: otc | Type: HUMAN OTC DRUG LABEL
Date: 20250527

ACTIVE INGREDIENTS: Isopropyl Alcohol 70 mL/100 mL
INACTIVE INGREDIENTS: Water

Drug Facts

Active Ingredient

Isopropyl Alcohol USP, 70% v/v

Purpose

Antiseptic

Use:

For preparation of the skin prior to injection; to decrease germs in minor cuts and scrapes.

Warnings:

For external use only. Flammable; keep away from fire and flame.

Keep out of reach of children. If swallowed, get medical help or contact a Poison Control Center immediately. Do not apply to irritated skin.

Do not use in the eyes, or on mucous membranes.

ASK DOCTOR

In case of deep or puncture wounds, consult a doctor. Do not use with electrocautery procedures.

Directions:

Open packet, remove pad and apply topically as needed on intended area until clean. Discard prep pad after single use.

Other information:

Store at room temperature. Sterile in unopened, undamaged package.

Inactive Ingredients:

Purified water

Principal Display Panel – Large 400 Count Carton Label

HCS

NDC 83506-005-01

Sterile, Pin Dot Texture
Alcohol Prep Pads

- For Individual, Professional, and Hospital use.
- Saturated with 70% v/v Isopropyl Alcohol
- 2-ply
- Use for skin preparation and cleansing
- Not made with natural rubber latex

Single Use Only

Large
400/box

Reorder Number 0207X4-AMA

Principal Display Panel – Large 400 Count Packet Label

HCS

Sterile, Pin Dot Texture
Alcohol
Prep Pads

- 70% v/v Isopropyl Alcohol
- 2-ply
- Not made with natural
  rubber latex

Large - Contains One Pad